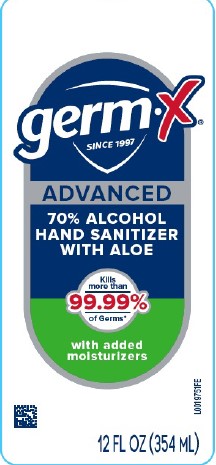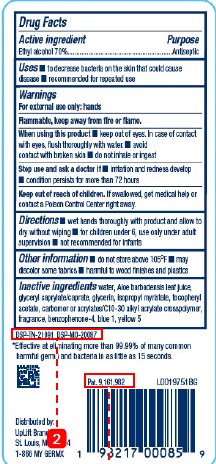 DRUG LABEL: Advanced Hand Sanitizer
NDC: 83986-439 | Form: GEL
Manufacturer: UpLift Brands LLC
Category: otc | Type: HUMAN OTC DRUG LABEL
Date: 20250226

ACTIVE INGREDIENTS: ALCOHOL 70 mL/100 mL
INACTIVE INGREDIENTS: SULISOBENZONE; FD&C BLUE NO. 1; FD&C YELLOW NO. 5; WATER; ALOE VERA LEAF; GLYCERYL CAPRYLATE/CAPRATE; GLYCERIN; ISOPROPYL MYRISTATE; .ALPHA.-TOCOPHEROL ACETATE; CARBOMER HOMOPOLYMER, UNSPECIFIED TYPE; ACRYLATES/C10-30 ALKYL ACRYLATE CROSSPOLYMER (60000 MPA.S)

Germ-X 439.001/439AB-AC rev1
Advanced Hand Sanitizer with Aloe

Active ingredient

Ethyl alcohol 70%

Purpose

Antiseptic

Uses

- to decrease bacteria on the skin that could cause disease
- recommended for repeated use

Warnings

For external use only: hands

Flammable. Keep away from fire or flame.

When using this product

- keep out of eyes. In case of contact with eyes, flush thoroughly with water.
- avoid contact with broken skin
- do not inhale or ingest

Stop use and ask a doctor if

- irritation and redness develop
- conditon persists for more than 72 hours

Keep out of reach of children.

If swallowed, get medical help or contact a Poison Control Center right away.

Directions

- wet hands thoroughly with product and allow to dry without wiping
- for children under 6, use only under adult supervision
- not recommended for infants

Other information

- do not store above 105⁰F
- may discolor some fabrics
- harmful to wood finishes and plastics

Inactive ingredients

water, Aloe barbadensis leaf juice, glyceryl caprylate/caprate, glycerin, isopropyl myristate, tocopheryl acetate, carbomer or acrylates/C10-30 alkyl acrylate crosspolymer, fragrance, benzophenone-4, blue 1, yellow 5

Disclaimer

DSP-TN-21091 DSP-MO-20087

*Effective at eliminating more than 99.99% of many common harmful germs and bacteria in as little as 15 seconds.

Adverse Reaction

Distributed by:

UpLift Brands, LLC

St. Louis, MO 63114

1-866 MY GERMX

Pat. 9,161,982

Principal display panel

germ-x®

SINCE 1997

ADVANCED

70% ALCOHOL HAND SANITIZER WITH ALOE

Kills more than 99.99% of Germs*

with added moisturizers

12 FL OZ (354 mL)